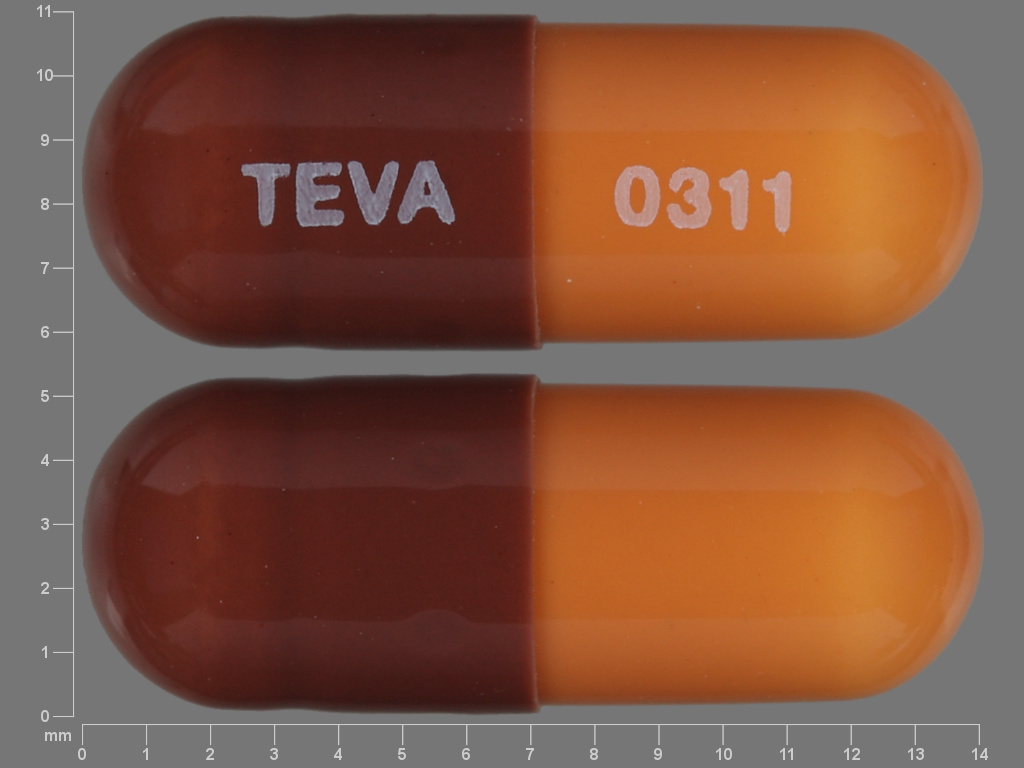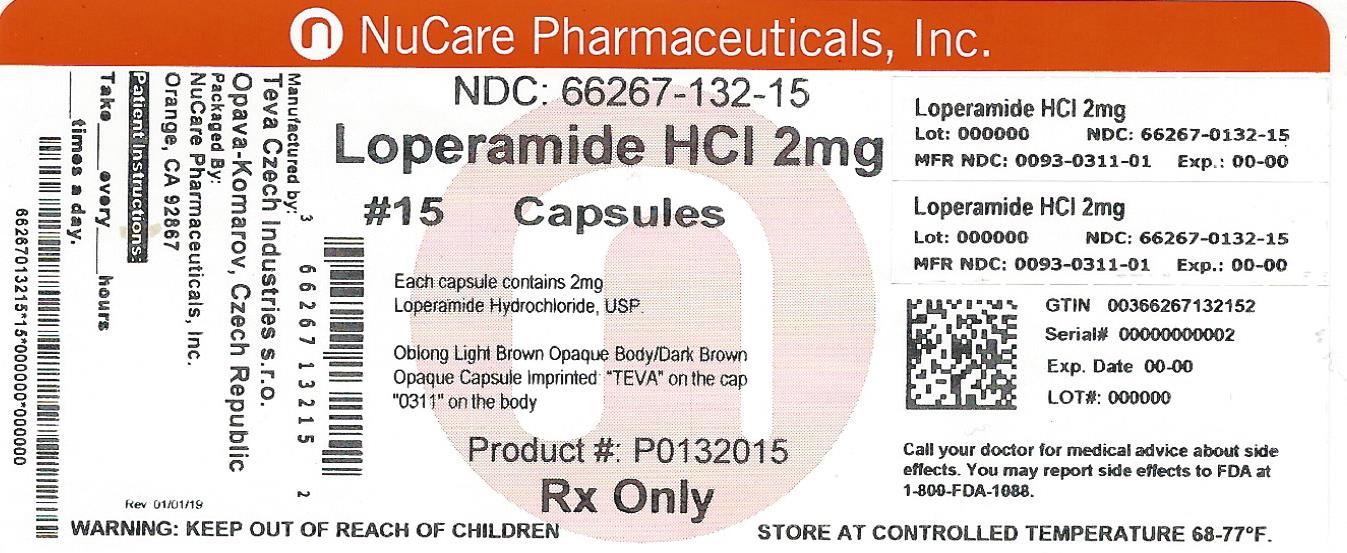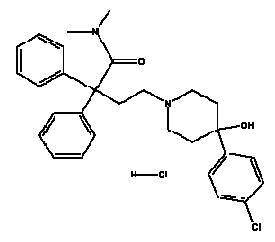 DRUG LABEL: Loperamide Hydrochloride
NDC: 66267-132 | Form: CAPSULE
Manufacturer: NuCare Pharmaceuticals, Inc.
Category: prescription | Type: HUMAN PRESCRIPTION DRUG LABEL
Date: 20240813

ACTIVE INGREDIENTS: LOPERAMIDE HYDROCHLORIDE 2 mg/1 1
INACTIVE INGREDIENTS: DIMETHICONE; GELATIN; FERROSOFERRIC OXIDE; FERRIC OXIDE RED; FERRIC OXIDE YELLOW; LACTOSE MONOHYDRATE; STARCH, CORN; MAGNESIUM STEARATE; SHELLAC; TITANIUM DIOXIDE

LOPERAMIDE HYDROCHLORIDE CAPSULES USP
0311
Rx only

DESCRIPTION

Loperamide hydrochloride is a white to slightly yellow powder and is freely soluble in methanol, isopropyl alcohol, chloroform and slightly soluble in water.

Loperamide hydrochloride, 4-(p-chlorophenyl)-4-hydroxy-N,N-dimethyl-α,α-diphenyl-1-piperidinebutyramide monohydrochloride, is a synthetic antidiarrheal for oral use. Its structural formula is:

C29H33ClN2O2•HCl M.W. 513.51

Loperamide hydrochloride is available in 2 mg capsules.

Each capsule, for oral administration, contains 2 mg loperamide hydrochloride. Loperamide hydrochloride capsules USP also contain the inactive ingredients: dimethylpolysiloxane, gelatin, iron oxide black, iron oxide red, iron oxide yellow, lactose monohydrate, pregelatinized corn starch, magnesium stearate, shellac, and titanium dioxide.

CLINICAL PHARMACOLOGY

In vitro and animal studies show that loperamide hydrochloride acts by slowing intestinal motility and by affecting water and electrolyte movement through the bowel. Loperamide binds to the opiate receptor in the gut wall. Consequently, it inhibits the release of acetylcholine and prostaglandins, thereby reducing peristalsis, and increasing intestinal transit time. Loperamide increases the tone of the anal sphincter, thereby reducing incontinence and urgency.

In man, loperamide hydrochloride prolongs the transit time of the intestinal contents. It reduces the daily fecal volume, increases the viscosity and bulk density, and diminishes the loss of fluid and electrolytes. Tolerance to the antidiarrheal effect has not been observed. Clinical studies have indicated that the apparent elimination half-life of loperamide hydrochloride in man is 10.8 hours with a range of 9.1 to 14.4 hours. Plasma levels of unchanged drug remain below 2 nanograms per mL after the intake of a 2 mg loperamide hydrochloride capsule. Plasma levels are highest approximately five hours after administration of the capsule and 2.5 hours after the liquid. The peak plasma levels of loperamide were similar for both formulations. Elimination of loperamide mainly occurs by oxidative N-demethylation. Cytochrome P450 (CYP450) isozymes, CYP2C8 and CYP3A4, are thought to play an important role in loperamide N-demethylation process since quercetin (CYP2C8 inhibitor) and ketoconazole (CYP3A4 inhibitor) significantly inhibited the N-demethylation process in vitro by 40% and 90%, respectively. In addition, CYP2B6 and CYP2D6 appear to play a minor role in loperamide N-demethylation. Excretion of the unchanged loperamide and its metabolites mainly occurs through the feces. In those patients in whom biochemical and hematological parameters were monitored during clinical trials, no trends toward abnormality during loperamide hydrochloride therapy were noted. Similarly, urinalyses, EKG and clinical ophthalmological examinations did not show trends toward abnormality.

INDICATIONS AND USAGE

Loperamide hydrochloride capsules are indicated for the control and symptomatic relief of acute nonspecific diarrhea and of chronic diarrhea associated with inflammatory bowel disease. Loperamide hydrochloride capsules are also indicated for reducing the volume of discharge from ileostomies.

CONTRAINDICATIONS

Loperamide hydrochloride capsules are contraindicated in patients with a known hypersensitivity to loperamide hydrochloride or to any of the excipients.

Loperamide hydrochloride is contraindicated in patients with abdominal pain in the absence of diarrhea.

Loperamide hydrochloride is not recommended in infants below 24 months of age.

Loperamide hydrochloride should not be used as the primary therapy:

1. in patients with acute dysentery, which is characterized by blood in stools and high fever,
2. in patients with acute ulcerative colitis,
3. in patients with bacterial enterocolitis caused by invasive organisms including Salmonella, Shigella, and Campylobacter,
4. in patients with pseudomembranous colitis associated with the use of broad-spectrum antibiotics.

WARNINGS

Fluid and electrolyte depletion often occur in patients who have diarrhea. In such cases, administration of appropriate fluid and electrolytes is very important. The use of loperamide hydrochloride does not preclude the need for appropriate fluid and electrolyte therapy.

In general, loperamide hydrochloride should not be used when inhibition of peristalsis is to be avoided due to the possible risk of significant sequelae including ileus, megacolon and toxic megacolon. Loperamide hydrochloride must be discontinued promptly when constipation, abdominal distention or ileus develop.

Treatment of diarrhea with loperamide hydrochloride is only symptomatic. Whenever an underlying etiology can be determined, specific treatment should be given when appropriate (or when indicated).

Patients with AIDS treated with loperamide hydrochloride for diarrhea should have therapy stopped at the earliest signs of abdominal distention. There have been isolated reports of toxic megacolon in AIDS patients with infectious colitis from both viral and bacterial pathogens treated with loperamide hydrochloride. {ref EDMS-PSDB-2564186, p. 12}

Loperamide hydrochloride should be used with special caution in young children because of the greater variability of response in this age group. Dehydration, particularly in younger children, may further influence the variability of response to loperamide hydrochloride.

PRECAUTIONS

General

Extremely rare allergic reactions including anaphylaxis and anaphylactic shock have been reported. In acute diarrhea, if clinical improvement is not observed in 48 hours, the administration of loperamide hydrochloride should be discontinued and patients should be advised to consult their physician. Although no pharmacokinetic data are available in patients with hepatic impairment, loperamide hydrochloride should be used with caution in such patients because of reduced first pass metabolism. Patients with hepatic dysfunction should be monitored closely for signs of CNS toxicity. No pharmacokinetic data are available in patients with renal impairment. Since it has been reported that the majority of the drug is metabolized and metabolites or the unchanged drug is excreted mainly in the feces, dosage adjustments in patients with renal impairment are not required. No formal studies have been conducted to evaluate the pharmacokinetics of loperamide in elderly subjects. However, in two studies that enrolled elderly patients, there were no major differences in the drug disposition in elderly patients with diarrhea relative to young patients.

Information for Patients

Patients should be advised to check with their physician if their diarrhea does not improve in 48 hours or if they note blood in their stools, develop a fever or develop abdominal distention.

Tiredness, dizziness, or drowsiness may occur in the setting of diarrheal syndromes treated with loperamide hydrochloride. Therefore, it is advisable to use caution when driving a car or operating machinery. (See ADVERSE REACTIONS.)

Drug Interactions

Nonclinical data have shown that loperamide is a P-glycoprotein substrate. Concomitant administration of loperamide (16 mg single dose) with a 600 mg single dose of either quinidine or ritonavir, both of which are P-glycoprotein inhibitors, resulted in a 2 to 3 fold increase in loperamide plasma levels. Due to the potential for enhanced central effects when loperamide is coadministered with quinidine and with ritonavir, caution should be exercised when loperamide is administered at the recommended dosages (2 mg, up to 16 mg maximum daily dose) with P-glycoprotein inhibitors.

When a single 16 mg dose of loperamide is coadministered with a 600 mg single dose of saquinavir, loperamide decreased saquinavir exposure by 54%, which may be of clinical relevance due to reduction of therapeutic efficacy of saquinavir. The effect of saquinavir on loperamide is of less clinical significance. Therefore, when loperamide is given with saquinavir, the therapeutic efficacy of saquinavir should be closely monitored.

Carcinogenesis, Mutagenesis, Impairment of Fertility

In an 18 month rat study with oral doses up to 40 mg/kg/day (21 times the maximum human dose of 16 mg/day, based on a body surface area comparison), there was no evidence of carcinogenesis.

Loperamide was not genotoxic in the Ames test, the SOS chromotest in E. coli, the dominant lethal test in female mice, or the mouse embryo cell transformation assay.

Fertility and reproductive performance was evaluated in rats using oral doses of 2.5, 10, and 40 mg/kg/day in one study, and 1, 5, 10, 20, and 40 mg/kg/day (females only) in a second study. Oral administration of 20 mg/kg/day (approximately 11 times the human dose based on a body surface area comparison) and higher produced strong impairment of female fertility. Treatment of female rats with up to 10 mg/kg/day p.o. (approximately 5 times the human dose based on a body surface area comparison) had no effect on fertility. Treatment of male rats with 40 mg/kg/day p.o. (approximately 21 times the human dose based on a body surface area comparison) produced impairment of male fertility, whereas administration of up to 10 mg/kg/day (approximately 5 times the human dose based on a body surface area comparison) had no effect.

Pregnancy

Teratogenic Effects

Pregnancy category C

Teratology studies have been performed in rats using oral doses of 2.5, 10, and 40 mg/kg/day, and in rabbits using oral doses of 5, 20, and 40 mg/kg/day. These studies have revealed no evidence of impaired fertility or harm to the fetus at doses up to 10 mg/kg/day in rats (5 times the human dose based on body surface area comparison) and 40 mg/kg/day in rabbits (43 times the human dose based on body surface area comparison). Treatment of rats with 40 mg/kg/day p.o. (21 times the human dose based on a body surface area comparison) produced marked impairment of fertility. The studies produced no evidence of teratogenic activity. There are no adequate and well-controlled studies in pregnant women. Loperamide should be used during pregnancy only if the potential benefit justifies the potential risk to the fetus.

Non-teratogenic Effects

In a peri- and post-natal reproduction study in rats, oral administration of 40 mg/kg/day produced impairment of growth and survival of offspring.

Nursing Mothers

Small amounts of loperamide may appear in human breast milk. Therefore, loperamide hydrochloride is not recommended during breast-feeding.

Pediatric Use

See the WARNINGS section for information on the greater variability of response in this age group.

In case of accidental overdosage of loperamide hydrochloride by pediatric patients, see OVERDOSAGE section for suggested treatment.

ADVERSE REACTIONS

Clinical Trial Data

The adverse effects reported during clinical investigations of loperamide hydrochloride are difficult to distinguish from symptoms associated with the diarrheal syndrome. Adverse experiences recorded during clinical studies with loperamide hydrochloride were generally of a minor and self-limiting nature. They were more commonly observed during the treatment of chronic diarrhea.

The adverse events reported are summarized irrespective of the causality assessment of the investigators.

1) Adverse events from 4 placebo-controlled studies in patients with acute diarrhea

The adverse events with an incidence of 1.0% or greater, which were reported at least as often in patients on loperamide hydrochloride as on placebo, are presented in the table below.

 | Acute Diarrhea
 | Loperamide Hydrochloride | Placebo
No. of treated patients | 231 | 236
Gastrointestinal AE%
Constipation | 2.6% | 0.8%

The adverse events with an incidence of 1.0% or greater, which were more frequently reported in patients on placebo than on loperamide hydrochloride were: dry mouth, flatulence, abdominal cramp and colic.

2) Adverse events from 20 placebo-controlled studies in patients with chronic diarrhea

The adverse events with an incidence of 1.0% or greater, which were reported at least as often in patients on loperamide hydrochloride as on placebo, are presented below in the table below.

 | Chronic Diarrhea
 | Loperamide Hydrochloride | Placebo
No. of treated patients | 285 | 277
Gastrointestinal AE%
Constipation | 5.3% | 0%
Central and peripheral nervous system AE%
Dizziness | 1.4% | 0.7%

The adverse events with an incidence of 1.0% or greater, which were more frequently reported in patients on placebo than on loperamide hydrochloride were: nausea, vomiting, headache, meteorism, abdominal pain, abdominal cramp and colic.

3) Adverse events from seventy-six controlled and uncontrolled studies in patients with acute or chronic diarrhea

The adverse events with an incidence of 1.0% or greater in patients from all studies are given in the table below.

 | Acute Diarrhea | Chronic Diarrhea | All Studies [All patients in all studies, including those in which it was not specified if the adverse events occurred in patients with acute or chronic diarrhea.]
No. of treated patients | 1913 | 1371 | 3740
Gastrointestinal AE%
Nausea | 0.7% | 3.2% | 1.8%
Constipation | 1.6% | 1.9% | 1.7%
Abdominal cramps | 0.5% | 3.0% | 1.4%

Postmarketing Experience

The following adverse events have been reported:

Skin and Subcutaneous Tissue Disorders

Rash, pruritus, urticaria, angioedema, and extremely rare cases of bullous eruption including erythema multiforme, Stevens-Johnson syndrome and Toxic Epidermal Necrolysis have been reported with use of loperamide hydrochloride.

Immune System Disorders

Isolated occurrences of allergic reactions and in some cases severe hypersensitivity reactions including anaphylactic shock and anaphylactoid reactions have been reported with the use of loperamide hydrochloride.

Gastrointestinal Disorders

Dry mouth, abdominal pain, distention or discomfort, nausea, vomiting, flatulence, dyspepsia, constipation, paralytic ileus, megacolon, including toxic megacolon (see CONTRAINDICATIONS and WARNINGS).

Renal and Urinary Disorders

Urinary retention.

Nervous System Disorders

Drowsiness, dizziness.

General Disorders and Administrative Site Conditions

Tiredness.

A number of the adverse events reported during the clinical investigations and postmarketing experience with loperamide are frequent symptoms of the underlying diarrheal syndrome (abdominal pain/discomfort, nausea, vomiting, dry mouth, tiredness, drowsiness, dizziness, constipation, and flatulence). These symptoms are often difficult to distinguish from undesirable drug effects.

DRUG ABUSE AND DEPENDENCE

Abuse

A specific clinical study designed to assess the abuse potential of loperamide at high doses resulted in a finding of extremely low abuse potential.

Dependence

Studies in morphine-dependent monkeys demonstrated that loperamide hydrochloride at doses above those recommended for humans prevented signs of morphine withdrawal. However, in humans, the naloxone challenge pupil test, which when positive indicates opiate-like effects, performed after a single high dose, or after more than two years of therapeutic use of loperamide hydrochloride, was negative. Orally administered loperamide hydrochloride capsules (loperamide formulated with magnesium stearate) are both highly insoluble and penetrate the CNS poorly.

OVERDOSAGE

In cases of overdosage, (including relative overdose due to hepatic dysfunction), urinary retention, paralytic ileus and CNS depression may occur. Children may be more sensitive to CNS effects than adults. Clinical trials have demonstrated that a slurry of activated charcoal administered promptly after ingestion of loperamide hydrochloride can reduce the amount of drug which is absorbed into the systemic circulation by as much as ninefold. If vomiting occurs spontaneously upon ingestion, a slurry of 100 grams of activated charcoal should be administered orally as soon as fluids can be retained.

If vomiting has not occurred, gastric lavage should be performed followed by administration of 100 grams of the activated charcoal slurry through the gastric tube. In the event of overdosage, patients should be monitored for signs of CNS depression for at least 24 hours.

If symptoms of overdose occur, naloxone can be given as an antidote. If responsive to naloxone, vital signs must be monitored carefully for recurrence of symptoms of drug overdose for at least 24 hours after the last dose of naloxone.

In view of the prolonged action of loperamide and the short duration (one to three hours) of naloxone, the patient must be monitored closely and treated repeatedly with naloxone as indicated. Since relatively little drug is excreted in the urine, forced diuresis is not expected to be effective for loperamide hydrochloride overdosage.

In clinical trials an adult who took three 20 mg doses within a 24 hour period was nauseated after the second dose and vomited after the third dose. In studies designed to examine the potential for side effects, intentional ingestion of up to 60 mg of loperamide hydrochloride in a single dose to healthy subjects resulted in no significant adverse effects.

DOSAGE AND ADMINISTRATION

(1 capsule = 2 mg)

Patients should receive appropriate fluid and electrolyte replacement as needed.

Acute Diarrhea

Adults

The recommended initial dose is 4 mg (two capsules) followed by 2 mg (one capsule) after each unformed stool. Daily dosage should not exceed 16 mg (eight capsules). Clinical improvement is usually observed within 48 hours.

Children

In children 2 to 5 years of age (20 kg or less), the non-prescription liquid formulation (loperamide hydrochloride for oral solution, 1 mg/5 mL) should be used; for ages 6 to 12, either loperamide hydrochloride capsules or loperamide hydrochloride for oral solution may be used. For children 2 to 12 years of age, the following schedule for capsules or liquid will usually fulfill initial dosage requirements:

Recommended First Day Dosage Schedule

Two to five years: 1 mg t.i.d. (3 mg daily dose) (13 to 20 kg)

Six to eight years: 2 mg b.i.d. (4 mg daily dose) (20 to 30 kg)

Eight to twelve years: 2 mg t.i.d. (6 mg daily dose) (greater than 30 kg)

Recommended Subsequent Daily Dosage

Following the first treatment day, it is recommended that subsequent loperamide hydrochloride doses (1 mg/10 kg body weight) be administered only after a loose stool. Total daily dosage should not exceed recommended dosages for the first day.

Chronic Diarrhea

Children

Although loperamide hydrochloride has been studied in a limited number of children with chronic diarrhea; the therapeutic dose for the treatment of chronic diarrhea in a pediatric population has not been established.

Adults

The recommended initial dose is 4 mg (two capsules) followed by 2 mg (one capsule) after each unformed stool until diarrhea is controlled, after which the dosage of loperamide hydrochloride capsules should be reduced to meet individual requirements. When the optimal daily dosage has been established, this amount may then be administered as a single dose or in divided doses.

The average daily maintenance dosage in clinical trials was 4 to 8 mg (two to four capsules). A dosage of 16 mg (eight capsules) was rarely exceeded. If clinical improvement is not observed after treatment with 16 mg per day for at least 10 days, symptoms are unlikely to be controlled by further administration. Loperamide hydrochloride capsules administration may be continued if diarrhea cannot be adequately controlled with diet or specific treatment.

Children Under 2 Years

The use of loperamide hydrochloride in children under 2 years is not recommended. There have been rare reports of paralytic ileus associated with abdominal distention. Most of these reports occurred in the setting of acute dysentery, overdose, and with very young children less than two years of age.

Elderly

No formal pharmacokinetic studies were conducted in elderly subjects. However, there were no major differences reported in the drug disposition in elderly patients with diarrhea relative to young patients. No dosage adjustment is required for the elderly.

Renal Impairment

No pharmacokinetic data are available in patients with renal impairment. Since the metabolites and the unchanged drug are mainly excreted in the feces, no dosage adjustment is required for patients with renal impairment (see PRECAUTIONS).

Hepatic Impairment

Although no pharmacokinetic data are available in patients with hepatic impairment, loperamide hydrochloride should be used with caution in such patients because of reduced first pass metabolism (see PRECAUTIONS).

HOW SUPPLIED

Loperamide hydrochloride capsules USP, 2 mg are available as:

A light brown opaque body and dark brown opaque capsule, imprinted "TEVA" on the cap and "0311" on the body and packaged in bottles of 12, 15, 18, 20, and 60.

Store at 20° to 25°C (68° to 77°F) [See USP Controlled Room Temperature].

Dispense in a well-closed container, as defined in the USP, with a child-resistant closure (as required).

KEEP THIS AND ALL MEDICATIONS OUT OF THE REACH OF CHILDREN.

Manufactured In Czech Republic By:

TEVA Czech Industries, s.r.o.

Opava-Komarov, Czech Republic

Manufactured For:

TEVA PHARMACEUTICALS USA, INC.

North Wales, PA 19454

Rev. N 9/2014